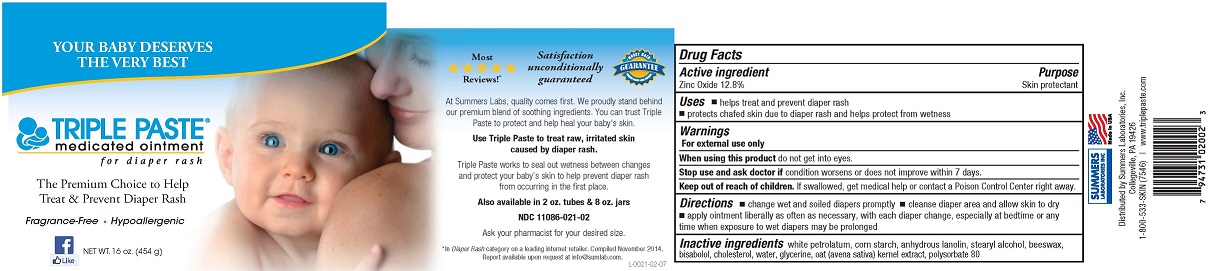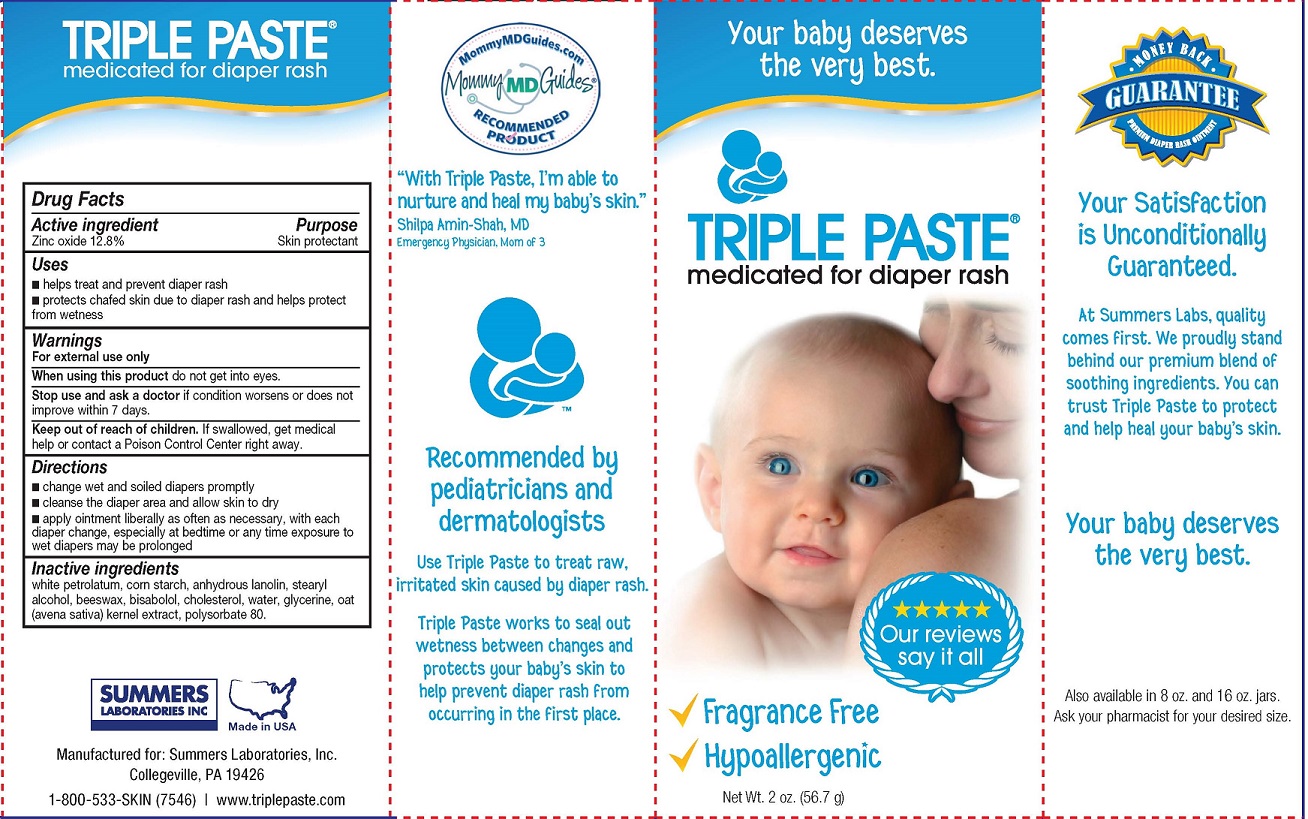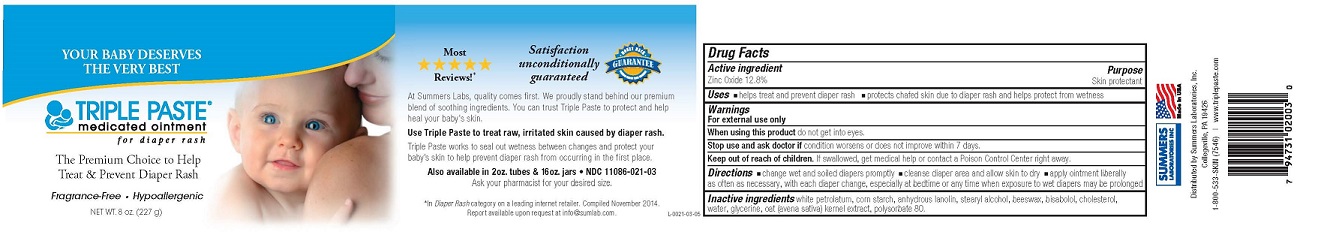 DRUG LABEL: TRIPLE
NDC: 11086-021 | Form: PASTE
Manufacturer: Summers Laboratories Inc
Category: otc | Type: HUMAN OTC DRUG LABEL
Date: 20231009

ACTIVE INGREDIENTS: ZINC OXIDE 12.8 g/100 g
INACTIVE INGREDIENTS: PETROLATUM; STARCH, CORN; LANOLIN; STEARYL ALCOHOL; YELLOW WAX 8 g/100 g; .ALPHA.-BISABOLOL, (+)-; CHOLESTEROL; WATER; GLYCERIN; OAT; POLYSORBATE 80

SUMMERS LABS (as PLD) - TRIPLE PASTE (11086-021)

ACTIVE INGREDIENT

ZINC OXIDE 12.8%

PURPOSE

SKIN PROTECTANT

USES

- HELPS TREAT AND PREVENT DIAPER RASH
- PROTECTS CHAFED SKIN DUE TO DIAPER RASH AND HELPS PROTECT FROM WETNESS

WARNINGS

FOR EXTERNAL USE ONLY

When using this product

- DO NOT GET INTO EYES

Stop and ask a doctor if

- condition worsens or does not improve within 7 days

KEEP OUT OF REACH OF CHILDREN. IF SWALLOWED, GET MEDICAL HELP OR CONTCT A POISON CONTROL CENTER RIGHT AWAY.

DIRECTIONS

- Change wet and soiled diapers promptly
- Cleanse the diaper area and allow skin to dry
- Apply ointment liberally as often as necessary, with each diaper change, especially at bedtime or any time exposure to wet diapers may be prolonged

INACTIVE INGREDIENTS

white petrolatum, corn starch, anhydrous lanolin, stearyl alcohol, beeswax, bisabolol, cholesterol, water, glycerine, oat (avena sativa) kernel extract, polysorbate 80.